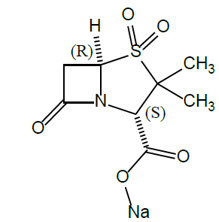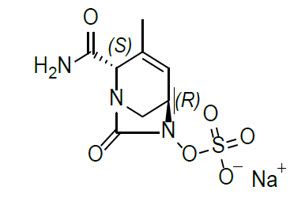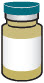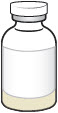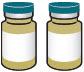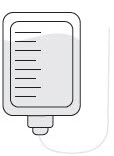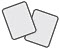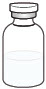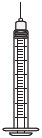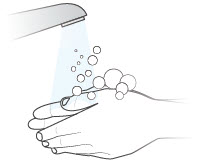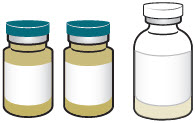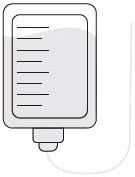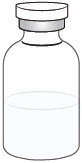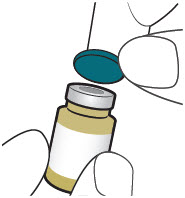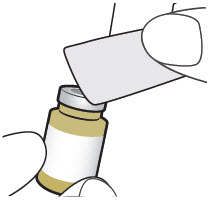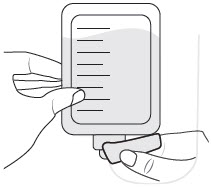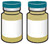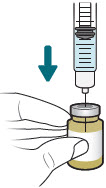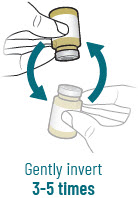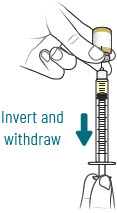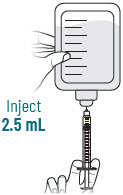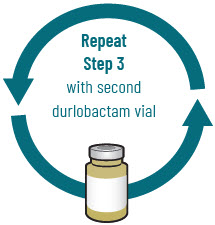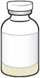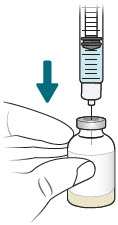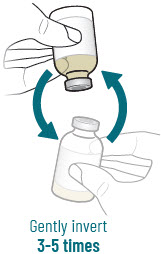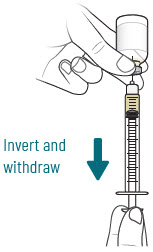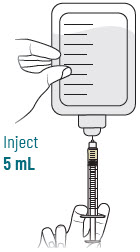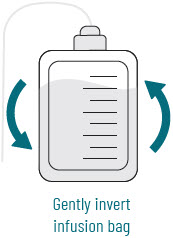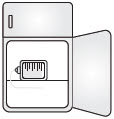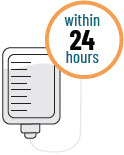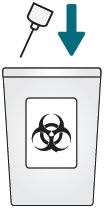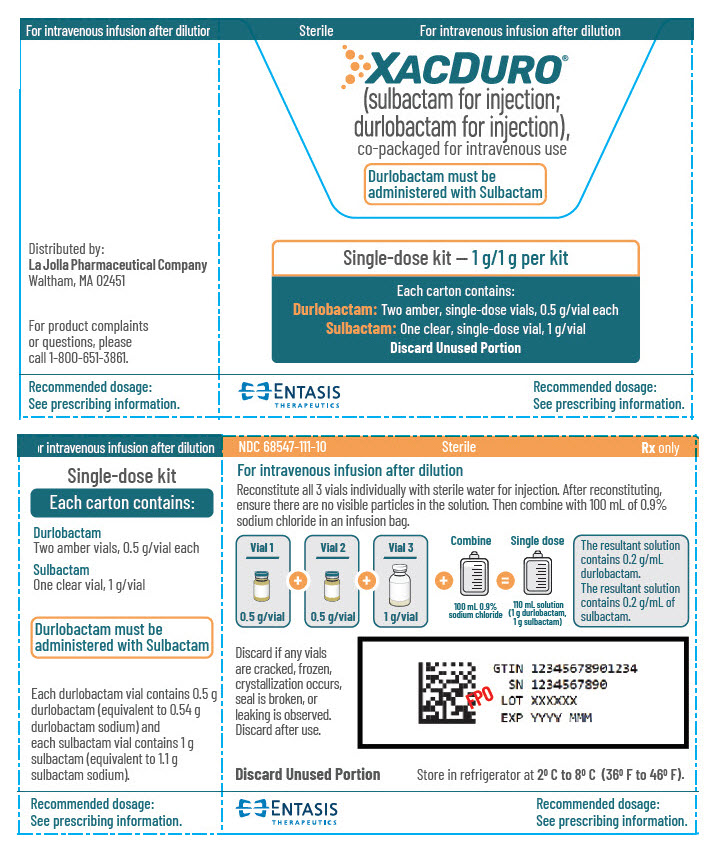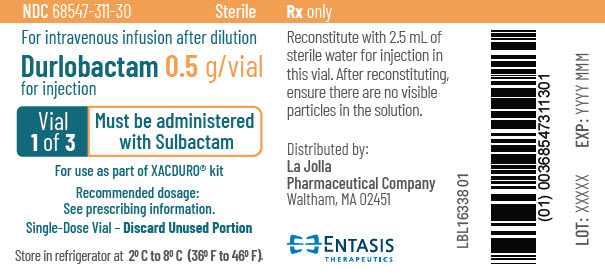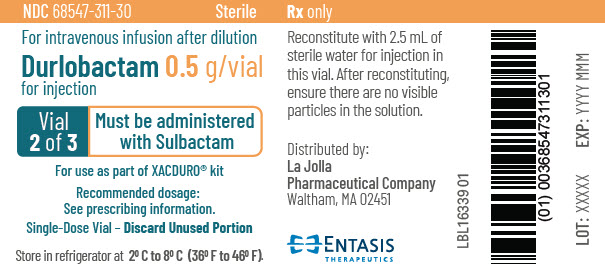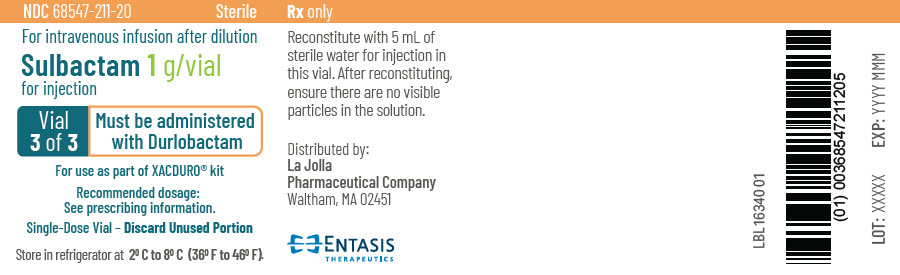 DRUG LABEL: Xacduro
NDC: 68547-111 | Form: KIT | Route: INTRAVENOUS
Manufacturer: La Jolla Pharmaceutical Company
Category: prescription | Type: HUMAN PRESCRIPTION DRUG LABEL
Date: 20251126

ACTIVE INGREDIENTS: sulbactam sodium 1 g/5 mL; durlobactam sodium 0.5 g/2.5 mL

HIGHLIGHTS OF PRESCRIBING INFORMATION

These highlights do not include all the information needed to use XACDURO safely and effectively. See full prescribing information for XACDURO.
XACDURO® (sulbactam for injection; durlobactam for injection), co-packaged for intravenous use
Initial U.S. Approval: 2023

1 INDICATIONS AND USAGE

XACDURO is a co-packaged product containing sulbactam, a beta-lactam antibacterial and beta lactamase inhibitor, and durlobactam, a beta lactamase inhibitor, indicated in patients 18 years of age and older for the treatment of hospital-acquired bacterial pneumonia and ventilator-associated bacterial pneumonia (HABP/VABP), caused by susceptible isolates of Acinetobacter baumannii-calcoaceticus complex. (1.1)

Limitations of Use:

XACDURO is not indicated for the treatment of HABP/VABP caused by pathogens other than susceptible isolates of Acinetobacter baumannii-calcoaceticus complex. (1.1, 14)

To reduce the development of drug-resistant bacteria and maintain the effectiveness of XACDURO and other antibacterial drugs, XACDURO should be used only to treat or prevent infections that are proven or strongly suspected to be caused by bacteria. (1.2)

2 DOSAGE AND ADMINISTRATION

- Administer XACDURO (1 g of sulbactam, 1 g of durlobactam) every 6 hours by intravenous (IV) infusion over 3 hours in patients with creatinine clearance (CLcr) of 45 to 129 mL/min. (2.1)
- Dosing regimen adjustments are recommended for CLcr less than 45 mL/min and CLcr greater than or equal to 130 mL/min. (2.2)
- Administer all doses of XACDURO by IV infusion over 3 hours. (2.3)
- See full prescribing information for instructions on the preparation of the intravenous solution. (2.4)

3 DOSAGE FORMS AND STRENGTHS

XACDURO is a co-packaged kit containing the following two components as sterile powders for reconstitution (3):

- 1 clear single-dose vial of sulbactam for injection 1 g and
- 2 amber single-dose vials of durlobactam for injection 0.5 g.

4 CONTRAINDICATIONS

Known history of severe hypersensitivity to the components of XACDURO (sulbactam and durlobactam), or other beta-lactam antibacterial drugs. (4)

5 WARNINGS AND PRECAUTIONS

- Hypersensitivity Reactions: Serious and occasionally fatal hypersensitivity (anaphylactic) reactions have been reported with beta-lactam antibacterial drugs. Hypersensitivity was observed in patients treated with XACDURO. If an allergic reaction occurs, discontinue XACDURO. (5.1)
- Clostridioides difficile-Associated Diarrhea (CDAD): CDAD has been reported with nearly all systemic antibacterial agents, including XACDURO. Evaluate if diarrhea occurs. (5.2)

6 ADVERSE REACTIONS

The most common adverse reactions (incidence > 10%) were liver test abnormalities, diarrhea, anemia, and hypokalemia. (6.1)

To report SUSPECTED ADVERSE REACTIONS, contact Entasis Therapeutics Inc. at 1-800-651-3861 or FDA at 1-800-FDA-1088 or www.fda.gov/medwatch.

7 DRUG INTERACTIONS

Organic Anion Transporter 1 (OAT1) Inhibitors: Concomitant administration with OAT1 inhibitors may increase plasma concentrations of XACDURO. Concomitant administration is not recommended. (7.1)

FULL PRESCRIBING INFORMATION

1 INDICATIONS AND USAGE

1.1 Hospital-acquired Bacterial Pneumonia and Ventilator-associated Bacterial Pneumonia (HABP/VABP)

XACDURO is indicated in patients 18 years of age and older for the treatment of hospital-acquired bacterial pneumonia and ventilator-associated bacterial pneumonia (HABP/VABP), caused by susceptible isolates of Acinetobacter baumannii-calcoaceticus complex.

Limitations of Use

XACDURO is not indicated for the treatment of HABP/VABP caused by pathogens other than susceptible isolates of Acinetobacter baumannii-calcoaceticus complex [see Clinical Studies (14)].

1.2 Usage

To reduce the development of drug-resistant bacteria and maintain the effectiveness of XACDURO and other antibacterial drugs, XACDURO should be used only to treat or prevent infections that are proven or strongly suspected to be caused by susceptible bacteria. When culture and susceptibility information are available, they should be considered in selecting or modifying antibacterial therapy. In the absence of such data, local epidemiology and susceptibility patterns may contribute to the empiric selection of therapy.

2 DOSAGE AND ADMINISTRATION

2.1 Recommended Dosage

XACDURO is a co-packaged product containing sulbactam for injection and durlobactam for injection. The recommended dosage of XACDURO is 1 gram (g) of sulbactam and 1 g of durlobactam every 6 hours administered by intravenous (IV) infusion over 3 hours in adults with a creatinine clearance (CLcr) of 45 to 129 mL/min.

Adjustments to the dosing regimen for XACDURO are recommended for patients with CLcr less than 45 mL/min and for patients with CLcr greater than or equal to 130 mL/min [see Dosage and Administration (2.2)].

The recommended duration of treatment with XACDURO is 7 to 14 days. The duration of therapy should be guided by the patient's clinical status.

2.2 Dosage in Patients (18 Years of Age and Older) Based on Renal Function

See Table 1 for the recommended dosage of XACDURO in patients (18 years of age and older) based on renal function [see Use in Specific Populations (8.6) and Clinical Pharmacology (12.3)].

Adjustments to the dosing regimen are recommended for patients with creatinine clearance (CLcr) less than 45 mL/min and patients with augmented renal clearance (CLcr greater than or equal to 130 mL/min). For patients undergoing intermittent hemodialysis (HD), start the dosing of XACDURO immediately after the completion of HD.

For patients with fluctuating renal function, monitor CLcr and adjust dosage accordingly [see Use in Specific Populations (8.6)].

Table 1: Dosage of XACDURO (Sulbactam and Durlobactam) in Patients (18 Years of Age and Older) Based on Renal Function
Dose of Sulbactam and Durlobactam (g) | Estimated CLcr (mL/min) [CLcr = creatinine clearance estimated by Cockcroft-Gault equation] | Frequency
sulbactam 1 g and durlobactam 1 g | Greater than or equal to 130 | Every 4 hours
sulbactam 1 g and durlobactam 1 g | 45 to 129 | Every 6 hours
sulbactam 1 g and durlobactam 1 g | 30 to 44 | Every 8 hours
sulbactam 1 g and durlobactam 1 g | 15 to 29 | Every 12 hours
sulbactam 1 g and durlobactam 1 g | less than 15 [For patients on hemodialysis, the dose should be administered after the dialysis session has ended] | For patients initiating XACDURO: Every 12 hours for the first 3 doses (0, 12, and 24 hours), followed by every 24 hours after the third dose For patients currently receiving XACDURO whose CLcr declines to less than 15 mL/min: Every 24 hours

2.3 Administration

The prepared XACDURO solution [see Dosage and Administration (2.4)] should be brought to ambient room temperature (over 15 to 30 min) prior to infusion to the patient. Administer all doses of XACDURO by intravenous (IV) infusion over 3 hours.

2.4 Preparation of XACDURO for Intravenous Administration

XACDURO is a co-packaged kit containing 1 clear single-dose vial of sulbactam 1g and 2 amber single-dose vials of durlobactam 0.5g as sterile powders that must be reconstituted and further diluted using aseptic technique prior to intravenous infusion.

XACDURO does not contain a bacteriostatic preservative and the prepared solution must be used within 24 hours when stored refrigerated at 2°C to 8°C (36°F to 46°F). Discard unused portion.

Items required to prepare XACDURO:

- XACDURO kit (includes one sulbactam 1 g single-dose vial and two durlobactam 0.5 g single-dose vials)
- 100 mL infusion bag containing 0.9% Sodium Chloride Injection, USP
- 10 mL Sterile Water for Injection, USP
- 10 mL sterile syringe and alcohol wipes

Preparation of XACDURO:

1. Reconstitute the sulbactam 1 g single-dose vial with 5 mL of Sterile Water for Injection and gently shake to dissolve. Each reconstituted vial contains 1 g of sulbactam per 5 mL of clear, colorless to slightly yellow solution. The reconstituted solution is not for direct injection and must be diluted before intravenous infusion. Dilution must occur within 1 hour of reconstitution.
2. Reconstitute each durlobactam 0.5 g single-dose vial with 2.5 mL of Sterile Water for Injection and gently shake to dissolve. Each reconstituted vial contains 0.5 g of durlobactam per 2.5 mL of clear, light yellow to orange solution. The reconstituted solution is not for direct injection and must be diluted before intravenous infusion. Dilution must occur within 1 hour of reconstitution.
3. To prepare the required XACDURO dose, withdraw 5 mL of reconstituted sulbactam and 5 mL (2.5 mL from each vial) of reconstituted durlobactam. Add the withdrawn volume of both sulbactam and durlobactam to a 100 mL infusion bag of 0.9% Sodium Chloride for Injection, USP. Discard unused portion.

Parenteral drug products should be inspected visually for particulate matter and discoloration prior to administration, whenever solution and container permit. The prepared XACDURO solution should appear as a clear, light yellow to orange solution, free of particulates. If the XACDURO solution is cloudy or contains particulates, do not administer.

2.5 Compatibility

XACDURO is compatible with 0.9% Sodium Chloride Injection, USP.

The compatibility of XACDURO for administration with solutions containing other drugs or other diluents has not been established. XACDURO should not be mixed with other drugs or physically added to solutions containing other drugs.

2.6 Storage of Prepared Solution in Infusion Bag

Store the prepared bag in the refrigerator at 2°C to 8°C (36°F to 46°F) until administration. The time between starting the reconstitution of the powders and the conclusion of the infusion should not exceed 24 hours. Do not freeze.

3 DOSAGE FORMS AND STRENGTHS

XACDURO is a co-packaged kit containing the following two components as sterile powders for reconstitution:

- 1 clear single-dose vial of sulbactam for injection 1g (as white to off-white powder) and
- 2 amber single-dose vials of durlobactam for injection 0.5g (as solid cake or powder) in each vial.

4 CONTRAINDICATIONS

XACDURO is contraindicated in patients with a history of known severe hypersensitivity to the components of XACDURO (sulbactam and durlobactam), or other beta-lactam antibacterial drugs [see Warnings and Precautions (5.1)].

5 WARNINGS AND PRECAUTIONS

5.1 Hypersensitivity Reactions

Serious and occasionally fatal hypersensitivity (anaphylactic) reactions and serious skin reactions have been reported in patients receiving beta-lactam antibacterial drugs. These reactions are more likely to occur in individuals with a history of beta-lactam hypersensitivity and/or a history of sensitivity to multiple allergens. Hypersensitivity was observed in patients treated with XACDURO in clinical trials [see Adverse Reactions (6.1)]. Before initiating therapy with XACDURO, careful inquiry should be made concerning previous hypersensitivity reactions to carbapenems, penicillins, cephalosporins, other beta lactams, and other allergens. Discontinue XACDURO if an allergic reaction occurs.

5.2 Clostridioides difficile-Associated Diarrhea (CDAD)

Clostridioides difficile-associated diarrhea (CDAD) has been reported with use of nearly all antibacterial agents, including XACDURO, and may range in severity from mild diarrhea to fatal colitis. Treatment with antibacterial agents alters the normal flora of the colon leading to overgrowth of C. difficile.

C. difficile produces toxins A and B which contribute to the development of CDAD. Hypertoxin producing strains of C. difficile cause increased morbidity and mortality, as these infections can be refractory to antimicrobial therapy and may require colectomy. CDAD must be considered in all patients who present with diarrhea following antibacterial drug use. Careful medical history is necessary since CDAD has been reported to occur over two months after the administration of antibacterial agents.

If CDAD is suspected or confirmed, the risk/benefit of continuing treatment with XACDURO should be assessed. Appropriate fluid and electrolyte management, protein supplementation, antibacterial drug treatment of C. difficile, and surgical evaluation should be instituted as clinically indicated.

5.3 Development of Drug-Resistant Bacteria

Prescribing XACDURO in the absence of a proven or strongly suspected bacterial infection or a prophylactic indication is unlikely to provide benefit to the patient and increases the risk of the development of drug-resistant bacteria.

6 ADVERSE REACTIONS

The following serious adverse reactions are described in greater detail in the Warnings and Precautions section:

- Hypersensitivity Reactions [see Warnings and Precautions (5.1)]
- Clostridioides difficile-Associated Diarrhea (CDAD) [see Warnings and Precautions (5.2)]

6.1 Clinical Trials Experience

Clinical trials are conducted under widely varying conditions, therefore adverse reaction rates observed in the clinical trials of a drug cannot be directly compared to rates in the clinical trials of another drug and may not reflect the rates observed in practice.

The safety of durlobactam with or without sulbactam was evaluated in 380 adult subjects across six phase 1 trials, one phase 2 trial in patients with complicated urinary tract infections (cUTIs) including acute pyelonephritis, and one phase 3 trial (also referred to as Trial 1) in adult patients with infections caused by Acinetobacter baumannii-calcoaceticus complex including hospital-acquired bacterial pneumonia (HABP), ventilator-associated bacterial pneumonia (VABP), and ventilated pneumonia (VP) [see Clinical Studies (14)].

In the randomized, active-controlled portion of the phase 3 trial, 91 patients received XACDURO (1 g sulbactam and 1 g durlobactam, or renally adjusted dose) intravenously over 3 hours every 6 hours and 86 patients were treated with colistin 2.5 mg/kg (or renally adjusted dose) intravenously over 30 minutes every 12 hours after an initial loading dose of colistin 2.5 to 5 mg/kg. Both treatment arms also received 1 g imipenem/1 g cilastatin (or renally adjusted dose) intravenously every 6 hours as background therapy for potential HABP/VABP pathogens other than Acinetobacter baumannii-calcoaceticus complex. The mean duration of XACDURO therapy was 9 days versus 8 days for colistin.

Serious Adverse Reactions and Discontinuation of Treatment

Thirty-six patients (40%) in the XACDURO treatment group and 42 patients (49%) in the colistin treatment group experienced serious adverse reactions. Discontinuation of treatment due to any adverse reaction occurred in 10/91 (11%) patients treated with XACDURO and in 14/86 (16%) patients treated with colistin. One patient treated with XACDURO developed anaphylactic shock which led to discontinuation of treatment.

Common Adverse Reactions

Adverse reactions were reported in 88% (80/91) of patients in the XACDURO treatment group and 94% (81/86) of patients in the colistin treatment group. The most common adverse reactions reported in >10% of patients treated with XACDURO were liver test abnormalities, diarrhea, anemia, and hypokalemia. Table 2 lists selected adverse reactions occurring at a frequency of >5% in Trial 1.

Table 2. Selected Adverse Reactions Occurring at a Frequency of >5% in Trial 1
Adverse Reaction | XACDURO (N=91) n (%) | Colistin (N=86) n (%)
Any Adverse Reaction | 80 (88) | 81 (94)
Liver test abnormalities [Liver test abnormalities includes the following adverse reactions: liver function test abnormal, hepatic function abnormal, increased transaminases, ALT increased, and AST increased; Acute kidney injury includes the following adverse reactions: renal impairment, blood Cr increased, toxic nephropathy, renal failure and acute kidney injury.] | 17 (19) | 18 (21)
Diarrhea | 15 (17) | 9 (11)
Anemia | 12 (13) | 12 (14)
Hypokalemia | 11 (12) | 9 (11)
Arrhythmia | 8 (9) | 8 (9)
Acute kidney injury | 5 (6) | 31 (36)
Thrombocytopenia | 5 (6) | 3 (4)
Constipation | 5 (6) | 5 (6)

7 DRUG INTERACTIONS

7.1 Organic Anion Transporter 1 (OAT1) Inhibitors

Concomitant administration with OAT1 inhibitors may increase plasma concentrations of sulbactam. Concomitant administration of OAT1 inhibitors (e.g., probenecid) with XACDURO is not recommended. [see Clinical Pharmacology (12.3)].

8 USE IN SPECIFIC POPULATIONS

8.1 Pregnancy

Risk Summary

XACDURO

There are no available data on the use of XACDURO in pregnancy to evaluate for a drug-associated risk of major birth defects, miscarriage, or other adverse maternal or fetal outcomes.

Individual Components of XACDURO

Sulbactam:

Available published data from case reports and case series with sulbactam use in combination with ampicillin during pregnancy over many decades have not identified a drug-associated risk of major birth defects, miscarriage or other adverse maternal or fetal outcomes. The published literature reports that sulbactam crosses the human placenta. Reproduction studies have been performed in mice, rats, and rabbits at doses up to ten (10) times the human dose and have revealed no evidence of harm to the fetus due to sulbactam (see Data).

Durlobactam:

There are no available data on the use of durlobactam in pregnancy to evaluate for a drug-associated risk of major birth defects, miscarriage, or other adverse maternal or fetal outcomes.

Durlobactam administered to pregnant mice and rats during organogenesis, showed no drug-induced fetal malformations but an increased incidence of skeletal variations was observed in mice at 2- and 4-times the Maximum Recommended Human Dose (MRHD) (see Data).

The background risk of major birth defects and miscarriage for the indicated population is unknown. All pregnancies have a background risk of birth defect, loss, or other adverse outcomes. In the U.S. general population, the estimated background risk of major birth defects and miscarriages in clinically recognized pregnancies is 2% to 4% and 15% to 20%, respectively.

Data

Animal Data

Sulbactam:

Reproduction studies have been performed in mice, rats, and rabbits at doses up to ten (10) times the human dose and have revealed no evidence of harm to the fetus due to sulbactam sodium/ampicillin sodium.

Durlobactam:

Daily administration of durlobactam at 400, 800, or 1600 mg/kg/day (administered as four doses per day) via subcutaneous injection to pregnant mice from gestation day (GD) 6 through 15 resulted in durlobactam-related, increased incidence of skeletal variations (unossified calcaneum) of the hindlimb and asymmetrical ossification of the sternebrae and supernumerary ribs at 800 and/or 1600 mg/kg, equivalent to 2- and 4-times the maximum recommended human dose based on area under the curve (AUC) comparisons. No adverse effects on mean body weight, reproductive performance, or cesarean section parameters were observed in any pregnant mice. IV infusion (2 hours/day) of durlobactam to pregnant female Sprague Dawley rats from GD 6 to weaning on Lactation Day 20 at a dose level of 300 or 1000 mg/kg/day was well tolerated with no adverse maternal effects in either group. Similarly, there was no adverse effect of maternal treatment in either group on embryo-fetal, perinatal or postnatal development up to 1000 mg/kg/day (approximately 4 times the MRHD based on AUC).

8.2 Lactation

Risk Summary

There are no data on the presence of durlobactam in human or animal milk. Sulbactam is present in human milk in low concentrations. Published data report sulbactam in breastmilk at an estimated maximum daily infant dose of 560 mcg/kg/day (1% to 2% of adult weight-adjusted dose), assuming mean milk consumption of 200 mL/kg/day. There are no data on the effects of XACDURO, sulbactam, or durlobactam on the breastfed infant or on milk production.

The developmental and health benefits of breastfeeding should be considered along with the mother's clinical need for XACDURO and any potential adverse effects on the breastfed child from XACDURO or from the underlying maternal condition.

8.4 Pediatric Use

The safety and effectiveness of XACDURO in pediatric patients younger than 18 years of age have not been established.

8.5 Geriatric Use

Of the 91 patients treated with XACDURO in Trial 1, 49 (54%) were 65 years of age and older, including 17 (19%) patients 76 years of age and older. Clinical studies of XACDURO did not include sufficient numbers of patients aged 65 and over to determine whether they respond differently than younger patients.

XACDURO is known to be substantially excreted by the kidney and elderly patients are more likely to have decreased renal function. Adjust dosing regimen for elderly patients based on renal function [see Dosage and Administration (2.2), Use in Specific Populations (8.6) and Clinical Pharmacology (12.3)].

8.6 Renal Impairment

Patients with CLcr 45 to 129 mL/min

No dosage adjustment of XACDURO is recommended in patients with CLcr 45 to 129 mL/min.

Patients with CLcr Less Than 45 mL/min Including Patients Receiving Intermittent HD

Adjustments to the XACDURO dosing regimen are required in patients with CLcr less than 45 mL/min. In patients requiring HD, complete HD at the latest possible time before the start of XACDURO dosing [see Dosage and Administration (2.2) and Clinical Pharmacology (12.3)]. Monitor renal function regularly and adjust the dosage of XACDURO accordingly as renal function may change during the course of therapy.

Patients Receiving Continuous Renal Replacement Therapy (CRRT)

Limited information is available to provide a dosage recommendation in this setting and therapy should be guided by the patient's clinical status. While on CRRT, a patient's residual renal function may change, which may warrant a change in XACDURO dosage. Monitor renal function regularly and adjust the dosage of XACDURO accordingly as renal function may change during the course of therapy.

Patients with CLcr 130 mL/min or Greater

CLcr 130 mL/min or greater may be seen in seriously ill patients who are receiving intravenous fluid resuscitation. Dosage adjustment of XACDURO is required in patients with CLcr 130 mL/min or greater [see Dosage and Administration (2.2) and Clinical Pharmacology (12.3)]. Monitor renal function regularly and adjust the dosage of XACDURO accordingly as renal function may change during the course of therapy.

8.7 Hepatic Impairment

The effects of hepatic impairment on the pharmacokinetics of sulbactam and durlobactam have not been evaluated. Hepatic impairment is not expected to alter the elimination of XACDURO as neither sulbactam nor durlobactam undergo substantial hepatic metabolism/excretion. Dosage adjustments are not necessary in patients with impaired hepatic function.

10 OVERDOSAGE

There is no information on the clinical signs and symptoms associated with an overdose of XACDURO. Neurological adverse reactions, including convulsions, may occur with the attainment of high CSF levels of beta-lactams. Sulbactam and durlobactam are removed by hemodialysis [see Clinical Pharmacology (12.3)]. No clinical information is available on the use of hemodialysis to treat overdosage.

11 DESCRIPTION

XACDURO (sulbactam for injection and durlobactam for injection) is an antibacterial co-packaged product containing sulbactam sodium, a penicillin derivative beta-lactam antibacterial and beta-lactamase inhibitor, and durlobactam sodium, a diazabicyclooctane beta-lactamase inhibitor, for intravenous administration.

Sulbactam Sodium

Sulbactam sodium is a beta-lactam antibacterial and a beta-lactamase inhibitor. Chemically, sulbactam sodium is sodium penicillinate sulfone; sodium (2S, 5R)-3,3-dimethyl-7-oxo-4-thia-1-azabicyclo [3.2.0] heptane-2-carboxylate 4,4-dioxide. Sulbactam is a white to off-white crystalline powder that is freely soluble in water and its empirical formula is C8H10NNaO5S with a molecular weight of 255.22.

Figure 1: Chemical structure of sulbactam sodium

Durlobactam Sodium

Durlobactam is a beta-lactamase inhibitor antibacterial drug. Chemically, durlobactam sodium is sodium (2S,5R)-2-carbamoyl-3-methyl-7-oxo-1,6-diazabicyclo[3.2.1]oct-3-en-6-yl sulfate. Durlobactam sodium is the pure (2S,5R)-enantiomer of the trans diastereoisomer. It is a white to yellow amorphous powder that is freely soluble in water. The empirical formula is C8H10N3NaO6S and the molecular weight (sodium salt) is 299.23.

Figure 2: Chemical structure of durlobactam sodium

XACDURO is supplied as a co-packaged kit containing three single-dose vials each containing sterile powder for reconstitution: one clear single-dose vial contains 1 g sulbactam (equivalent to 1.1 g sulbactam sodium) and two amber single-dose vials each contain 0.5 g durlobactam (equivalent to 0.54 g durlobactam sodium) together with sodium hydroxide and hydrochloric acid used for pH adjustment.

12 CLINICAL PHARMACOLOGY

12.1 Mechanism of Action

XACDURO is an antibacterial drug [see Microbiology (12.4)].

12.2 Pharmacodynamics

For sulbactam, the percent time of dosing interval that unbound plasma concentrations of sulbactam exceed the minimum inhibitory concentration (MIC) of A. baumannii has been shown to be the best predictor of efficacy in animal and in vitro models of infection. For durlobactam, the ratio of the 24-hour unbound plasma durlobactam AUC to the sulbactam-durlobactam MIC (fAUC0–24/MIC) best predicts the activity in in vivo and in vitro models of infection.

Cardiac Electrophysiology

At a dose 4 times the maximum recommended single dose, durlobactam does not prolong the QTc interval to any clinically relevant extent.

12.3 Pharmacokinetics

Sulbactam and durlobactam pharmacokinetics are similar following single- and multiple-dose administrations. The Cmax and AUC of sulbactam increase in proportion to dose (0.5 times the recommended single dose to 1 g single dose). Durlobactam demonstrated dose-proportional pharmacokinetics across the dose range studied (0.25 times the recommended single dose to 2 times the recommended single dose infused over 3 hours every 6 hours).

The pharmacokinetic properties of the components of XACDURO and the pharmacokinetic parameters of sulbactam and durlobactam are summarized in Table 3.

Table 3: Pharmacokinetic Properties (Mean ± SD) of the Components of XACDURO
Pharmacokinetic Parameters | Sulbactam | Durlobactam
Cmax (µg/mL) [Pharmacokinetic parameters are presented at steady state (Day 3) in patients with normal renal function defined as creatinine clearance of greater than or equal to 90 mL/min and less than 130 mL/min at a dosage of 1 g sulbactam and 1 g durlobactam every 6 hours.] | 32.4 ± 24.7 | 29.2 ± 13.2
AUC0-24 (h∙µg/mL) | 515 ± 458 | 471 ± 240
Distribution
% Bound to human plasma protein | 38% | 10%
AUC0-6 ELF/plasma ratio | 0.5 | 0.37
Vss (L) | 25.4 ± 11.3 | 30.3 ± 12.9
Metabolism | Minimally metabolized
Elimination
CL (L/h) | 11.6 ± 5.64 | 9.96 ± 3.11
T1/2 (h) | 2.15 ± 1.16 | 2.52 ± 0.77
Excretion
Major route of elimination | Renal
% excreted unchanged in urine | 75% to 85% | 78%
AUC0-6 = area under the plasma concentration time curve from time of dosing to 6 hours post dose; AUC0-24 = area under the plasma concentration time curve from time of dosing to 24 hours; CL = clearance; Cmax = maximum concentration; ELF = epithelial lining fluid; SD = standard deviation, T1/2 = terminal half-life; Vss = volume of distribution at steady state

Specific Populations

No clinically significant differences in the pharmacokinetics of sulbactam or durlobactam were observed based on age (18-91 years), gender, weight (35-150 kg), and race (White, Black, Asian, American Indian/Alaska Native, Other).

Patients with Renal Impairment

In a single-dose trial evaluating the effect of renal impairment on the pharmacokinetics of sulbactam and durlobactam, dose normalized systemic exposures of sulbactam and durlobactam were higher at all levels of renal impairment compared to healthy subjects with CLcr greater than or equal to 90 mL/min (Table 4). In subjects with end stage renal disease (ESRD) on hemodialysis, the fraction of the dose removed by hemodialysis was 0.41 and 0.33 for sulbactam and durlobactam, respectively.

Table 4: Dose Normalized Fold AUC Increase in Subjects with Renal Impairment Compared to Subjects with CLcr ≥90 mL/min
Estimated eGFR (mL/min/1.73 m^2) | Sulbactam | Durlobactam
≥60 to <90 | 1.4 | 1.4
≥30 to <60 | 2.0 | 1.9
<30 | 4.3 | 3.7

To maintain systemic exposures similar to patients with normal renal function, dosage adjustment is recommended for patients with renal impairment. Patients on hemodialysis should receive XACDURO after hemodialysis session [see Dosage and Administration (2.2), Specific Populations (8.6)].

Patients with CLcr 130 mL/min or Greater

Increased sulbactam and durlobactam clearance have been observed in patients with CLcr of 130 mL/min or greater. A XACDURO (1.0 g sulbactam and 1.0 g durlobactam) dose every 4 hours infused over 3 hours provided sulbactam and durlobactam exposures comparable to those in patients with CLcr 90 to 129 mL/min [see Dosage and Administration (2.2), Use in Specific Populations (8.6)].

Patients with Hepatic Impairment

Sulbactam and durlobactam are primarily cleared renally; therefore, hepatic impairment is not likely to have any effect on XACDURO exposures [see Use in Specific Populations (8.7)].

Drug Interaction Studies

Clinical Studies

No drug-drug interactions were observed among durlobactam, sulbactam, imipenem, and cilastatin in a clinical study in healthy subjects.

In Vitro Studies Where Drug Interaction Potential Was Not Further Evaluated Clinically Cytochrome P450 (CYP) Enzymes: At therapeutic plasma concentrations, durlobactam does not inhibit CYP1A2, CYP2A6, CYP2B6, CYP2C8, CYP2C9, CYP2C19, CYP2D6, CYP2E1, or CYP3A4. Durlobactam showed no potential for in vitro induction of CYP1A2, CYP2B6, or CYP3A4.

No in vitro studies with CYP450 and sulbactam were conducted.

Membrane Transporter Systems:

In vitro data showed that sulbactam did not inhibit P-gp, BCRP, OATP1B1, OATP1B3, OCT1, OCT2, BSEP, OAT1, OAT3, MATE1, or MATE2-K at therapeutic plasma concentrations. In vitro data also indicated that durlobactam did not inhibit P-gp, BCRP, OATP1B1, OAT1, OAT3, or OCT2 at therapeutic plasma concentrations. Sulbactam and durlobactam are both substrates of OAT1. However, only sulbactam is predicted to have active secretion as a significant portion of total clearance; therefore, inhibition of OAT1 may increase sulbactam plasma concentrations. No clinical studies have been conducted with XACDURO and OAT1 inhibitors [see Drug Interactions (7.1)].

12.4 Microbiology

Mechanism of Action

XACDURO is a co-packaged product containing sulbactam and durlobactam. Sulbactam is a beta-lactam antibacterial and Ambler Class A serine beta-lactamase inhibitor that has bactericidal activity due to its inhibition of Acinetobacter baumannii-calcoaceticus complex (ABC) penicillin-binding proteins PBP1 and PBP3, which are essential enzymes required for bacterial cell wall synthesis.

Durlobactam is a diazabicyclooctane non-beta-lactam, beta-lactamase inhibitor, that protects sulbactam from degradation by certain serine-beta-lactamases. Durlobactam alone does not have antibacterial activity against ABC isolates.

XACDURO demonstrated in vitro activity against ABC isolates expressing serine beta-lactamases included in Ambler Class A (CTX-M-, TEM-, PER- and SHV-type extended spectrum beta-lactamases [ESBLs], KPC carbapenemase) Class C (ADC-type) and broad spectrum activity against Class D (OXA-type) enzymes.

Resistance

Mechanisms of beta-lactam resistance in ABC isolates may include either the production of beta-lactamases, modification of PBPs or target alteration, up-regulation of efflux pumps or loss of outer membrane porin.

XACDURO is not active against ABC isolates that produce Ambler Class B metallo-beta-lactamases or have modification of active target site of sulbactam (i.e., PBPs). Isolates may also produce in combination multiple beta-lactamases, express varying levels of beta-lactamases, have amino acid PBPs sequence variations or other resistance mechanisms that may contribute to resistance.

Interaction with Other Antimicrobials

In vitro studies showed no antagonism between XACDURO and other antibacterial drugs including ceftazidime-avibactam, imipenem, meropenem, amikacin, colistin, cefepime, ciprofloxacin, minocycline, rifampicin, rifaximin, daptomycin, dalbavancin, oritavancin, tedizolid, fidaxomicin, vancomycin, linezolid, metronidazole, and fluconazole.

Animal Models of Infection

Durlobactam restored activity of sulbactam in animal models of infection (including neutropenic mouse thigh and lung infections) against XACDURO-susceptible A. baumannii strains.

Antimicrobial Activity

XACDURO has been shown to be active against most isolates of the following microorganisms both in vitro and in clinical infections [see Indications and Usage (1.1)].

Acinetobacter baumannii-calcoaceticus complex

Susceptibility Testing

For specific information regarding susceptibility test interpretive criteria and associated test methods and quality control standards recognized by FDA for XACDURO, please see: https://www.fda.gov/STIC.

13 NONCLINICAL TOXICOLOGY

13.1 Carcinogenesis, Mutagenesis, Impairment of Fertility

Carcinogenesis

Carcinogenicity studies with XACDURO have not been conducted.

Mutagenesis

Durlobactam was negative in genetic toxicology studies including the Salmonella typhimurium bacterial reverse mutation assay, in vivo and in vitro micronucleus assays, and the in vivo Pig-A assay in rats.

Genetic toxicology studies were not conducted with sulbactam or the combination of sulbactam-durlobactam.

Impairment of Fertility

No adverse effects on fertility, reproductive performance, fetal viability, growth, or postnatal development were observed in male and female rats, and female mice for durlobactam at intravenous doses up to 1000 mg/kg/day (approximately 4 times the MRHD based on AUC comparisons) and subcutaneous doses up to 1600 mg/kg/day, (equivalent to 4 times the MRHD based on AUC comparisons) respectively.

14 CLINICAL STUDIES

Treatment of Hospital-acquired and Ventilator-associated Bacterial Pneumonia Caused by Acinetobacter baumannii-calcoaceticus Complex Organisms

A total of 177 hospitalized adults with documented Acinetobacter baumannii-calcoaceticus complex infections were randomized and treated in a multicenter, active-controlled, investigator-unblinded, independent assessor-blinded, non-inferiority, phase 3 trial (Trial 1, NCT03894046). Patients were treated with either XACDURO (1 g sulbactam and 1 g durlobactam, or renally adjusted dose) intravenously over 3 hours every 6 hours (n = 91) or colistin 2.5 mg/kg (or renally adjusted dose) intravenously over 30 minutes every 12 hours after an initial loading dose of colistin 2.5 to 5 mg/kg (n = 86). Both treatment arms also received 1 g imipenem/1 g cilastatin (or renally adjusted dose) intravenously every 6 hours as background therapy for potential HABP/VABP pathogens other than Acinetobacter baumannii-calcoaceticus complex. Patients received up to 14 days of therapy.

The primary efficacy endpoint for the study was 28-day all-cause mortality in the patients who received any amount of study medication with a confirmed baseline infection with carbapenem-resistant Acinetobacter baumannii-calcoaceticus complex (CRABC microbiologically modified intent to treat (m-MITT) population). Among 128 patients in the CRABC m-MITT population, 125 patients who did not withdraw consent prior to assessment of survival status at Day 28 were assessed: 63 patients in the XACDURO group and 62 patients in the colistin group.

The demographic and baseline characteristics were comparable between treatment groups among 125 patients in the analysis: 74% male, 50% White, and 44% Asian; the mean age was 63 (±17) years. The majority of patients had pneumonia as the baseline infection (53% VABP and 43% HABP); 2% had bacteremia. The mean Acute Physiology and Chronic Health Evaluation II (APACHE II) score at baseline was 17, and 26% of patients had an APACHE II score ≥ 20. At randomization, 64% of patients had been in the ICU ≥5 days, 26% of patients had been in the ICU for >14 days, and 75% were mechanically ventilated. Approximately 39% of patients had CLcr less than 90 mL/min at baseline. The mean duration of treatment was 9 days for the XACDURO group and 8 days for the colistin group.

Table 5 shows results for the primary endpoint of Day 28 all-cause mortality in the CRABC m-MITT population. XACDURO was non-inferior to colistin with regard to Day 28 all-cause mortality.

Table 5: All-cause Mortality at Day 28 (CRABC m-MITT Population)
 | XACDURO n/N [Percentage was calculated using N, the number of patients in the specified population, as the denominator.] (%) | Colistin n/N (%) | Treatment Difference (95% CI) [The 95% CI (2-sided) was computed using a continuity-corrected z statistic.]
Day 28 All-Cause Mortality | 12/63 (19.0%) | 20/62 (32.3%) | -13.2% (-30.0, 3.5)
CI = Confidence Interval

Clinical cure rates were also evaluated. Clinical cure was defined as complete resolution or significant improvement of signs and symptoms that were present at baseline and no new symptoms, such that no additional gram-negative antimicrobial therapy was warranted. Clinical cure rates in the CRABC m-MITT population at the Test of Cure (TOC) Visit that was 7 days (±2 days) after the end of treatment were 39/63 (61.9%) for XACDURO versus 25/62 (40.3%) for colistin.

16 HOW SUPPLIED/STORAGE AND HANDLING

16.1 How Supplied

XACDURO is a co-packaged product containing sulbactam for injection and durlobactam for injection. XACDURO is supplied as a kit (NDC 68547-111-10) containing the following single-dose vials each containing sterile powder for reconstitution:

- 1 g sulbactam in one clear glass single-dose vial
- 1 g durlobactam in two amber glass single-dose vials (0.5 g durlobactam in each single-dose vial)

Stoppers are not made with natural rubber latex.

16.2 Storage and Handling

XACDURO vials should be stored refrigerated at 2°C to 8°C (36°F to 46°F); brief exposure to 8°C to 15°C (46°F to 59°F) permitted [see USP Controlled Cold Temperature]. Do not freeze. Store prepared XACDURO solution in the refrigerator [see Dosage and Administration (2.6)].

17 PATIENT COUNSELING INFORMATION

Serious Allergic Reactions

Advise the patient, their families, or caregivers that allergic reactions, including serious allergic reactions, could occur and that serious reactions require immediate treatment. Ask them about any previous hypersensitivity reactions to XACDURO (sulbactam and durlobactam), other beta-lactams (including cephalosporins) or other allergens [see Warnings and Precautions (5.1)].

Potentially Serious Diarrhea

Advise the patient, their families, or caregivers that diarrhea is a common problem caused by antibacterial drugs, including XACDURO. Sometimes, frequent watery or bloody diarrhea may occur and may be a sign of a more serious intestinal infection. If severe watery or bloody diarrhea develops, tell them to contact their healthcare provider [see Warnings and Precautions (5.2)].

Antibacterial Resistance

Patients should be counseled that antibacterial drugs, including XACDURO, should only be used to treat bacterial infections. They do not treat viral infections (e.g., the common cold). Patients should be told that the medication should be administered exactly as directed. [see Warnings and Precautions (5.3)].

Distributed by:
La Jolla Pharmaceutical Company, Waltham, MA 02451

XACDURO is a registered trademark of Entasis Therapeutics Ltd.
Copyright ©2023, Entasis Therapeutics Ltd. All rights reserved.

INSTRUCTIONS FOR USE

XACDURO® (sulbactam for injection; durlobactam for injection), co-packaged for intravenous use 1 g/1 g per dose Single-dose kit 3 vials |  | Durlobactam 0.5 g/vial
XACDURO® (sulbactam for injection; durlobactam for injection), co-packaged for intravenous use 1 g/1 g per dose Single-dose kit 3 vials |  | Durlobactam 0.5 g/vial
XACDURO® (sulbactam for injection; durlobactam for injection), co-packaged for intravenous use 1 g/1 g per dose Single-dose kit 3 vials |  | Sulbactam 1 g/vial
This Instructions for Use provides information for preparing all 3 vials as a single dose.
Read this Instructions for Use before using this vial kit and prior to each use.

Important Information
Before Injecting

Important Information

- For intravenous use only
- Always use aseptic technique
- Ensure carton and vials are stored in refrigerator at 2° C to 8° C (36° F to 46° F)
- DO NOT use the supplies if damaged. This includes the vials, syringes, sterile water for injection vial, and infusion bag

For product complaints or questions, please call 1-800-651-3861.

Supplies
Included with kit: | Non-kit components:
(2) Durlobactam 0.5 g/vials |  | 100 mL of 0.9% sodium chloride infusion bag
(1) Sulbactam 1 g/vial | Alcohol wipes | Sterile water for injection | Syringe

1 Prepare Supplies

a. Use aseptic technique.
b. Prepare a clean, flat working surface.
c. Open kit and inspect that:
  - Vials are not damaged
  - Expiration date on carton and all three vials has not passed
d. Retrieve a full 100 mL infusion bag of 0.9% sodium chloride.
e. Retrieve a vial of sterile water for injection.

a.

c.

d.

e.

2 Clean Supplies

a. Remove all vial caps from the three vials and sterile water for injection.
b. Clean all the stoppers with alcohol wipe.
c. Clean infusion bag port of entry and surrounding area with alcohol wipe.

a.

b.

c.

Failure to clean could result in loss of sterility.

3

Reconstitute and Inject Both Durlobactam Vials (Vials 1 of 3 and 2 of 3)

a. Inject 2.5 mL of sterile water for injection into durlobactam vial.

b. Reconstitute the powder by gently inverting durlobactam vial back and forth 3-5 times. Hold vial base up to a light source to ensure the lyophilized powder is dissolved after inverting.

a.

b.

c.

d.

e.

After reconstituting, ensure there are no visisble particles in the solution.

c. Insert needle into durlobactam vial and gently invert vial to withdraw 2.5 mL.
d. Inject 2.5 mL of durlobactam into infusion bag.
e. Repeat step 3 with second vial of durlobactam.

4

Reconstitute and Inject Sulbactam Vial (Vial 3 of 3)

a. Inject 5 mL of sterile water for injection into sulbactam vial.
b. Reconstitute the powder by gently inverting sulbactam vial back and forth 3-5 times. Hold vial base up to a light source to ensure the powder is dissolved after inverting.

a.

b.

c.

d.

After reconstituting, ensure there are no visible particles in the solution.

c. Insert needle into sulbactam vial and gently invert vial to withdraw 5 mL.
d. Inject 5 mL of sulbactam into infusion bag.

5 Prepare Infusion Bag; a. Gently invert infusion bag to mix contents. |  | 6 Store Infusion Bag; a. Store infusion bag in refrigerator at 2° C to 8° C (36° F to 46° F). DO NOT freeze. b. Infusion time is 3 hours. Complete the infusion within 24 hours of reconstitution. | a. | 7 Dispose of Materials; a. Discard needle into sharps container. b. Discard syringe in waste container after needle is removed. c. Discard vials and all packaging in waste container.
 |  | Note: Before infusing, allow 15-30 minutes for infusion bag to reach room temperature after removing from refrigerator. | b.

XACDURO® is a registered trademark of Entasis Therapeutics Limited.

© 2023 Entasis Therapeutics. All rights reserved.

INS16343 01 Approved 2023 MAY

PRINCIPAL DISPLAY PANEL - Kit Carton

Sterile
For intravenous infusion after dilution

XACDURO®
(sulbactam for injection;
durlobactam for injection),
co-packaged for intravenous use

Durlobactam must be
administered with Sulbactam

Single-dose kit – 1 g/1 g per kit

Each carton contains:
Durlobactam: Two amber, single-dose vials, 0.5 g/vial each
Sulbactam: One clear, single-dose vial, 1 g/vial
Discard Unused Portion

ENTASIS
THERAPEUTICS

Recommended dosage:
See prescribing information.

PRINCIPAL DISPLAY PANEL - 0.5 g Vial Label - 1 of 3

NDC 68547-311-30
Sterile

For intravenous infusion after dilution

Durlobactam 0.5 g/vial
for injection

Vial
1 of 3

Must be administered
with Sulbactam

For use as part of XACDURO® kit

Recommended dosage:
See prescribing information.

Single-Dose Vial - Discard Unused Portion

Store in refrigerator at 2° C to 8° C (36° F to 46° F).

PRINCIPAL DISPLAY PANEL - 0.5 g Vial Label - 2 of 3

NDC 68547-311-30
Sterile

For intravenous infusion after dilution

Durlobactam 0.5 g/vial
for injection

Vial
2 of 3

Must be administered
with Sulbactam

For use as part of XACDURO® kit

Recommended dosage:
See prescribing information.

Single-Dose Vial - Discard Unused Portion

Store in refrigerator at 2° C to 8° C (36° F to 46° F).

PRINCIPAL DISPLAY PANEL - 1 g Vial Label

NDC 68547-211-20
Sterile

For intravenous infusion after dilution

Sulbactam 1 g/vial
for injection

Vial
3 of 3

Must be administered
with Durlobactam

For use as part of XACDURO® kit

Recommended dosage:
See prescribing information.

Single-Dose Vial - Discard Unused Portion

Store in refrigerator at 2° C to 8° C (36° F to 46° F).